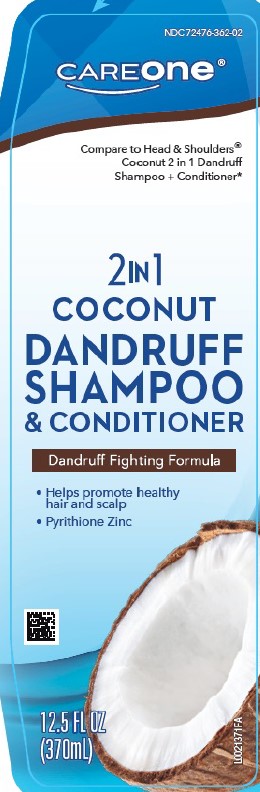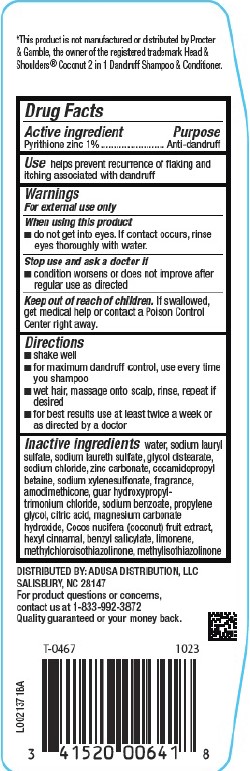 DRUG LABEL: 2 in 1 Dandruff
NDC: 72476-362 | Form: SHAMPOO
Manufacturer: Retail Business Services, LLC
Category: otc | Type: HUMAN OTC DRUG LABEL
Date: 20260206

ACTIVE INGREDIENTS: PYRITHIONE ZINC 10 mg/1 mL
INACTIVE INGREDIENTS: WATER; SODIUM LAURYL SULFATE; SODIUM LAURETH SULFATE; GLYCOL DISTEARATE; SODIUM CHLORIDE; ZINC CARBONATE; COCAMIDOPROPYL BETAINE; SODIUM XYLENESULFONATE; AMODIMETHICONE (800 CST); GUAR HYDROXYPROPYLTRIMONIUM CHLORIDE (1.7 SUBSTITUENTS PER SACCHARIDE); SODIUM BENZOATE; PROPYLENE GLYCOL; CITRIC ACID MONOHYDRATE; MAGNESIUM CARBONATE HYDROXIDE; COCONUT; HEXYL CINNAMATE; BENZYL SALICYLATE; LIMONENE, (+)-; METHYLCHLOROISOTHIAZOLINONE; METHYLISOTHIAZOLINONE

Care One 362.000/362AA-AB
Coconut Dandruff 2 in 1 Shampoo & Conditioner

Disclaimer

*This product is not manufactured or distributed by Procter & Gamble, the owner of the registered trademark Head & Shoulders® Coconut 2 in 1 Dandruff Shampoo & Conditioner.

Active ingredient

Pyrithione zinc 1%

Purpose

Anti-dandruff

Use

helps prevent recurrence of flaking and itching associated with dandruff

Warnings

For external use only

When using this product

- do not get into eyes. If contact occurs, rinse eyes thoroughly with water.

Stop use and ask a doctor if

- condition worsens or does not improve after regular use as directed

Keep out of reach of children.

If swallowed, get medical help or contact a Poison Control Center right away.

Directions

- shake well
- for maximum dandruff control, use every time you shampoo
- wet hair, massage onto scalp, rinse, repeat if desired
- for best results use at least twice a week or as directed by a doctor

Inactive ingredients

water, sodium lauryl sulfate, sodium laureth sulfate, glycol distearate, sodium chloride, zinc carbonate, cocamidopropyl betaine, sodium xylenesulfonate, fragrance, amodimethicone, guar hydroxypropyltrimonium chloride, sodium benzoate, propylene glycol, citric acid, magnesium carbonate hydroxide, Cocos nucifera (coconut) fruit extract, hexyl cinnamal, benzyl salicylate, limonene, methylchloroisothiazolinone, methylisothiazolinone

Adverse Reactions

DISTRIBUTED BY: ADUSA DISTRIBUTION, LLC

SALISBURY, NC 28147

For product questions or concerns, contact us at 1-833-922-3872

Quality guaranteed or your money back.

Principal Panel Display

NDC 72476-362-02

CAREone®

Compare to Head & Shoulders®Coconut 2 in 1 Dandruff Shampoo + Conditioner*

2 IN 1 Coconut Dandruff Shampoo & Conditioner

Dandruff Fighting Formula

- Helps promote healthy hair and scalp
- Pyrithione Zinc

12.5 FL OZ (370 mL)